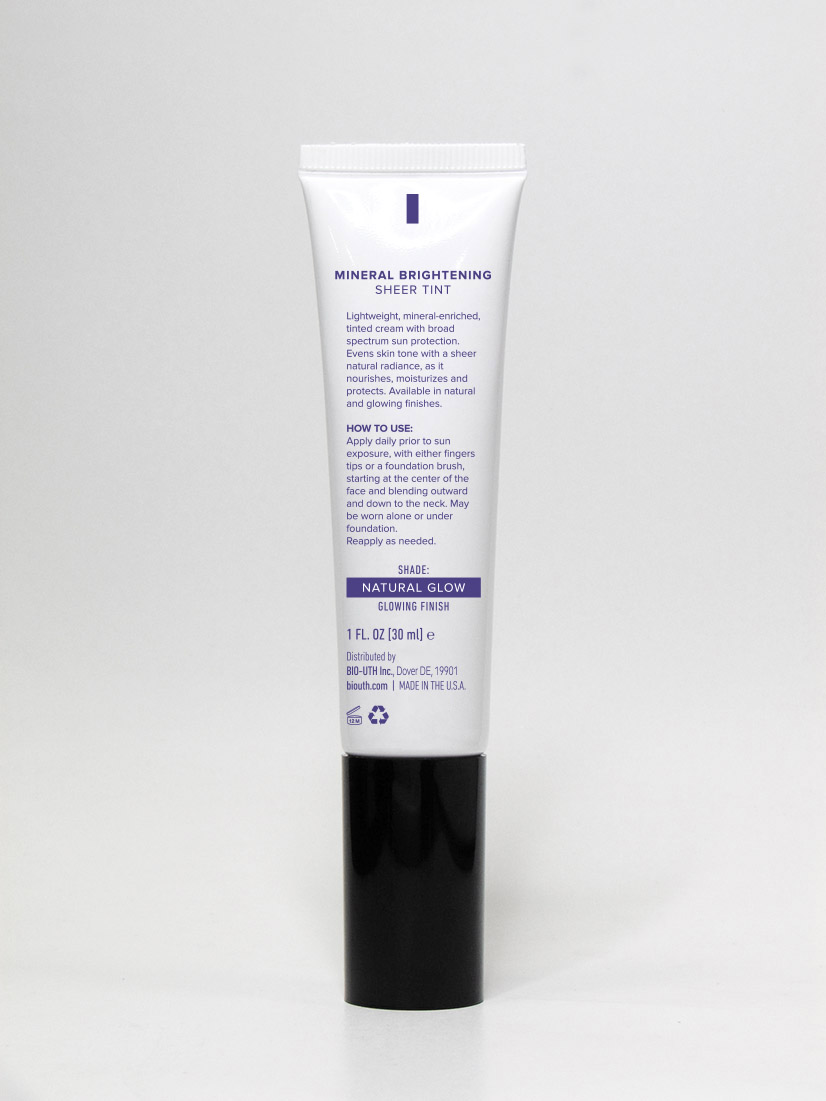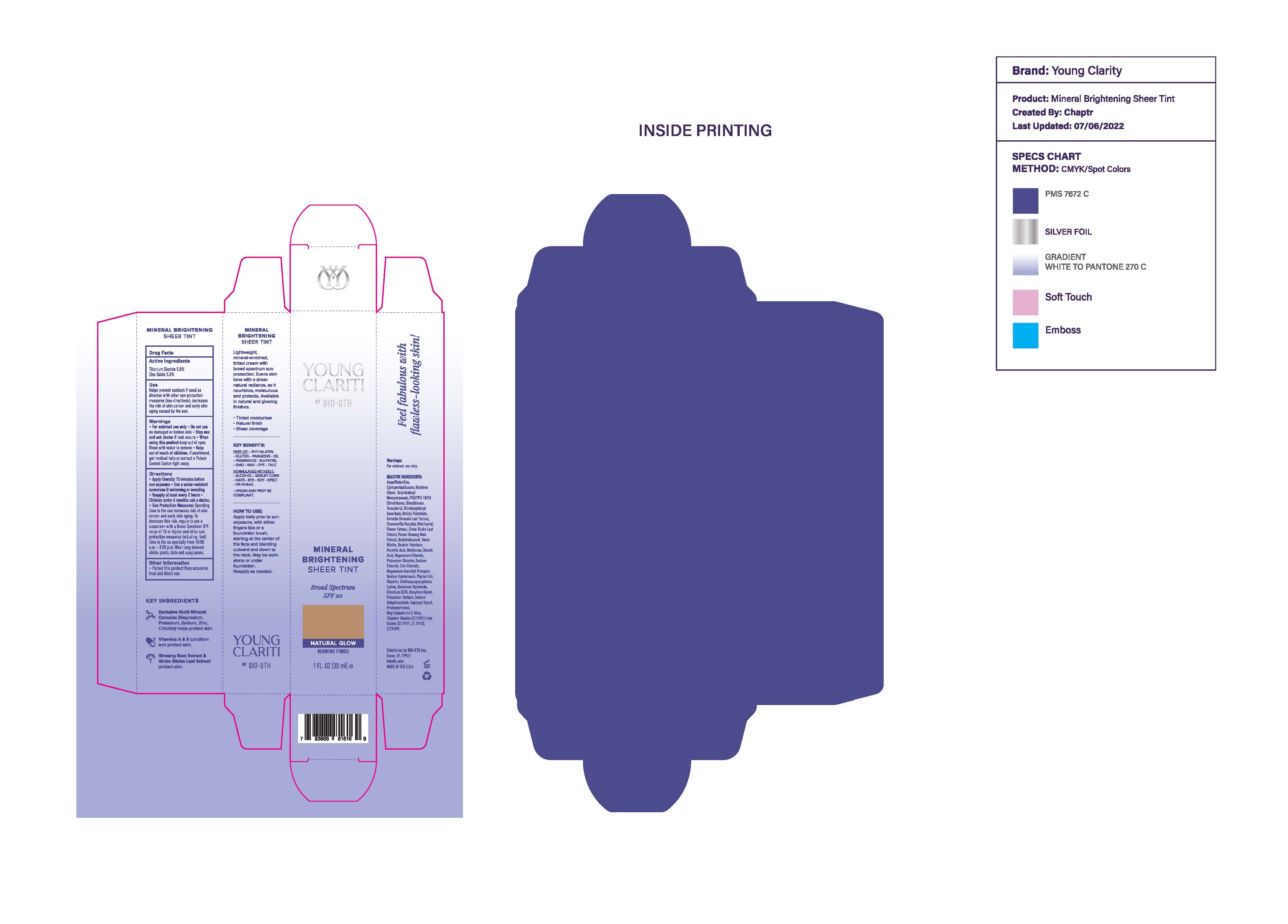 DRUG LABEL: YOUNG CLARITI MINERAL BRIGHTENING SHEER TINT BROADSPECTRUM SPF 20
NDC: 59735-851 | Form: CREAM
Manufacturer: MANA Products , Inc.
Category: otc | Type: HUMAN OTC DRUG LABEL
Date: 20240104

ACTIVE INGREDIENTS: TITANIUM DIOXIDE 5 g/30 mL; ZINC OXIDE 5 g/30 mL
INACTIVE INGREDIENTS: PHENOXYETHANOL; POTASSIUM SORBATE; PEG/PPG-18/18 DIMETHICONE; PALMITIC ACID; OCTYLDODECANOL; MAGNESIUM ASCORBYL PHOSPHATE; PHYTANTRIOL; DEXTRIN PALMITATE (CORN; 20000 MW); HEXYLENE GLYCOL; TOCOPHEROL; OCTYLDODECYL NEOPENTANOATE; FERRIC OXIDE YELLOW; FERROSOFERRIC OXIDE; EDETATE DISODIUM; GLYCERIN; ALUMINUM HYDROXIDE; SODIUM DEHYDROACETATE; FERRIC OXIDE RED; ZINC CHLORIDE; ASIAN GINSENG; METHICONE (20 CST); POTASSIUM CHLORIDE; CYCLOMETHICONE 5; CAPRYLYL GLYCOL; MICA; WATER; GINKGO; DIMETHICONE; TETRAHEXYLDECYL ASCORBATE; SODIUM CHLORIDE; HYALURONIC ACID (NON-ANIMAL STABILIZED); VITAMIN A PALMITATE; LYSINE; STEARIC ACID; BORON NITRIDE; MAGNESIUM CHLORIDE; BUTYLENE GLYCOL; GREEN TEA LEAF; CHAMOMILE; TRIETHOXYCAPRYLYLSILANE

Young Clariti Mineral Brightening Sheer Tint Broad Spectrum SPF 20- Natural Glow

Active Ingredients

Titanium Dioxide 5.00%

Zinc Oxide 5.00%

Purpose

Sunscreen Agent

Use

Helps prevent sunburn.
If used as directed with other sun protection measures (see Directions), decreases the risk of skin cancer and early skin aging caused by the sun.

Warnings

For external use only
Do not use on damaged or broken skin
When using this product keep out of eyes. Rinse with water to remove.

Directions

Apply liberally 15 minutes before sun exposure
Reapply at least every 2 hours
Use water resistant sunscreen if swimming or sweating
Sun Protection Measures: Spending time in the sun increases risk of skin cancer and early aging. To decrease this risk, regular use of a sunscreen with a Broad Spectrum SPF value of 15 or higher and other sun protection measures including: Limit time in the sun especially from 10:00 am - 2:00 pm. Wear long sleeved shirts, pants, hats and sunglasses.
Children under 6 months: ask a doctor

Inactive Ingredients

Aqua/Water /Eau, Cyclopentasiloxane,Butylene Glycol, Octyldodecyl Neopentanoate, PEG/PPG-18/18 Dimethicone, Dimethicone,

Tocopherol, Tetrahexyldecyl Ascorbate,Retinyl Palmitate,Camellia Sinensis Leaf Extract, Chamomilla Recutita (Matricaria) Flower Extract, Ginko Biloba Leaf Extract, Panax Ginsing Root Extract, Octyldodecanol, Boron Nitride, Dextrin Palmitate, Palmitic Acid, Methicone, Stearic Acid, Magnesium Chloride, Potassium Chloride, Sodium Chloride, Zinc Chloride,Magnesium Ascorbyl Phosphate, Sodium Hyaluronate, Phytantriol, Glycerin, Triethoxycaprylylsilane,Lysine, Aluminum Hydroxide,Disodium EDTA,Hexylene Glycol, Potassium Sorbate, Sodium Dehydroacetate, Caprylyl Glycol, Phenoxyethanol. May Contain (+/-): Mica, Titanium (CI 77891), Iron Oxides (CI 77491,CI 77492, CI 77499).

Other Information

Protect this product from excessive heat and direct sun

Stop use and ask a doctor if rash occurs.

RECENT MAJOR CHANGES

dosage & admin update

Keep out of reach of children. If swallowed, get medical help or contact a Poison Control Center right away.